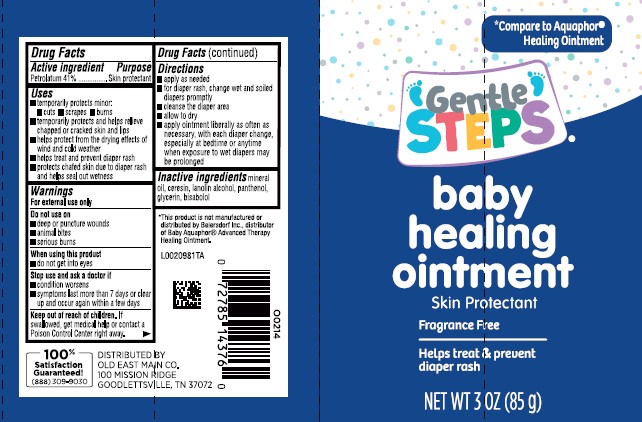 DRUG LABEL: Healing  for Babies
NDC: 55910-180 | Form: OINTMENT
Manufacturer: Old East Main Co.
Category: otc | Type: HUMAN OTC DRUG LABEL
Date: 20260302

ACTIVE INGREDIENTS: PETROLATUM 410 mg/1 g
INACTIVE INGREDIENTS: MINERAL OIL; CERESIN; LANOLIN ALCOHOLS; PANTHENOL; GLYCERIN; LEVOMENOL

Gentle Steps 180.000/180AC
Healing Ointment for Babies

Active ingredient

Petrolatum 41%

Purpose

Skin Protectant

Uses

- temporarily protects minor: •cuts •scrapes burns
- temporarily protects and helps relieve chapped or cracked skin and lips
- helps protect from the drying effects of wind and cold weather
- helps treat and prevent diaper rash
- protects chafed skin due to diaper rash and helps seal out wetness

Warnings

For external use only

Do not use on

- deep or puncture wounds
- animal bites
- serious burns

When using this product

- do not get into eyes

Stop use and ask a doctor if

- condition worsens
- symptom last more than 7 days or clear up and occur again within a few days

Keep out of reach of children.

If swallowed, get medical help or contact a Poison Control Center right away.

Directions

- apply as needed
- for diaper rash, change wet and soiled diapers promptly
- cleanse the diaper area
- allow to dry
- apply ointment liberally as often as necessary, with each diaper change, especially at bedtime or anytime when exposure to wet diapers may be prolonged

Inactive ingredients

mineral oil, ceresin, lanolin alcohol, panthenol, glycerin, bisabolol

ADVERSE REACTION

*This product is not manufactured or distributed by Beiersdorf, Inc., distributor of Baby AquaphorAdvanced Therapy Healing Ointment.

100% Satisfaction Guaranteed!

(888)309-9030

DISTRIBUTED BY

OLD EAST MAIN CO

100 MISSION RIDGE

GOODLETTSVILLE, TN 37072

principal display panel

*Compare to Aquaphor®Healing Ointment

Gentle Steps®

baby healing ointment

Skin Protectant

Fragrance Free

Helps treat & prevent diaper rash

NET WT 3 OZ (85 g)